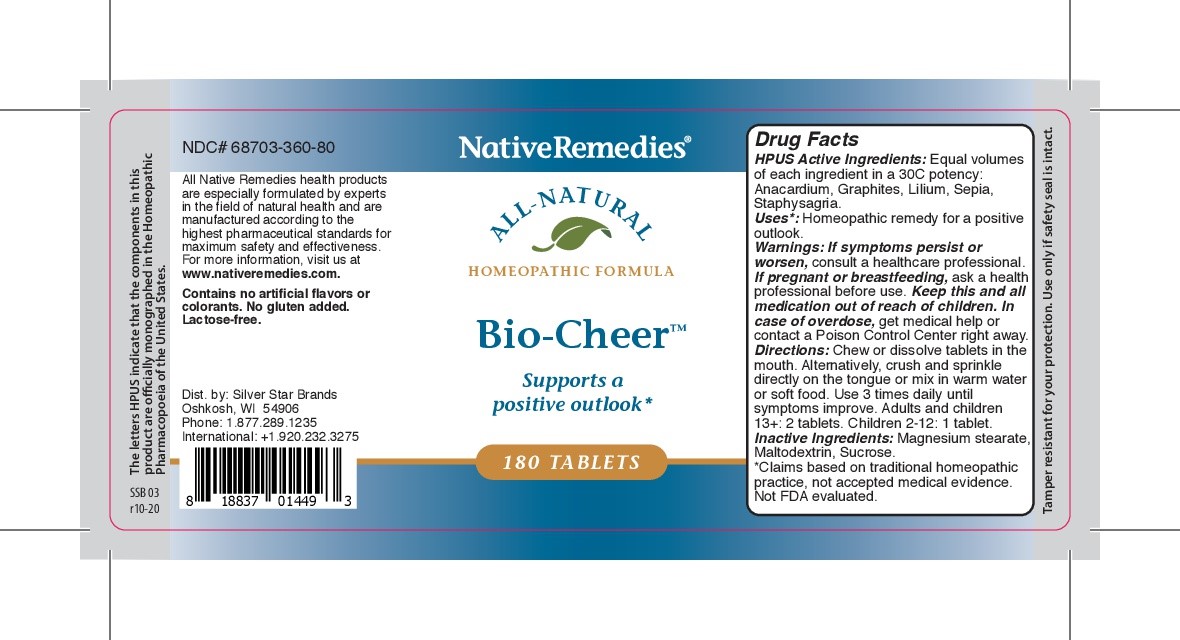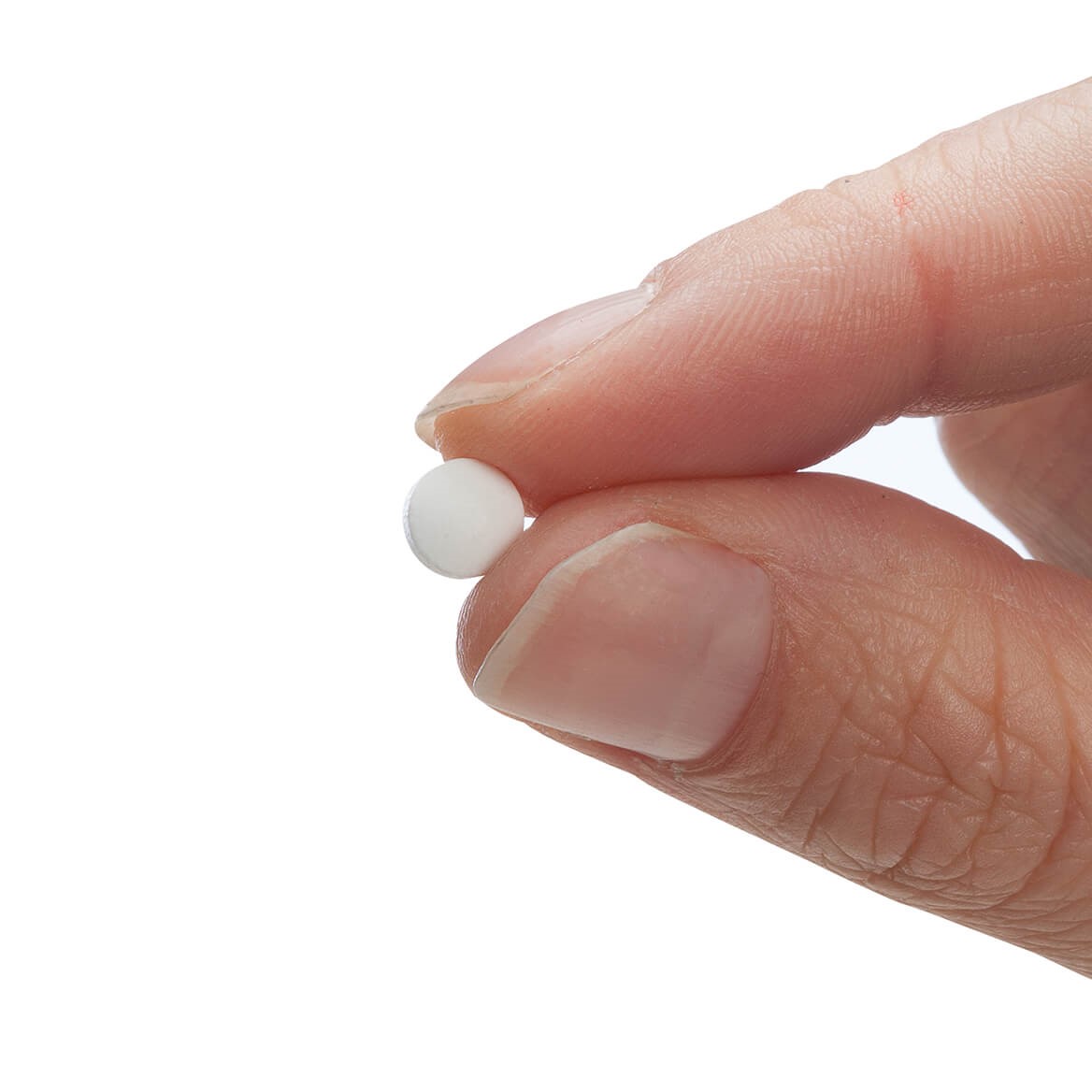 DRUG LABEL: Bio-cheer
NDC: 68703-360 | Form: TABLET
Manufacturer: Silver Star Brands
Category: homeopathic | Type: HUMAN OTC DRUG LABEL
Date: 20201229

ACTIVE INGREDIENTS: SEPIA OFFICINALIS JUICE 30 [hp_C]/180 1; DELPHINIUM STAPHISAGRIA SEED 30 [hp_C]/180 1; LILIUM LANCIFOLIUM BULB 30 [hp_C]/180 1; ANACARDIUM OCCIDENTALE FRUIT 30 [hp_C]/180 1; GRAPHITE 30 [hp_C]/180 1
INACTIVE INGREDIENTS: MALTODEXTRIN; SUCROSE; MAGNESIUM STEARATE

NativeRemedies® Bio-Cheer™

HPUS Active Ingredients: Anacardium, Graphites, Lilium, Sepia, Staphysagria.

Uses*

Uses*: Homeopathic remedy for a positive outlook.

*Claims based on traditional homeopathic practice, not accepted medical evidence. Not FDA evaluated.

Warnings

Warnings: If symptoms persist or worsen, consult a healthcare professional. If pregnant or breastfeeding, ask a health professional before use. Keep this and all medication out of reach of children. In case of overdose, get medical help or contact a Poison Control Center right away.

Directions

Directions: Chew or dissolve tablets in the mouth. Alternatively, crush and sprinkle directly on th etongue or mix in warm water or soft food. Use 3 times daily until symptoms improve. Adults and children 13+: 2 tablets. Children 2-12 1 tablet.

OTHER SAFETY INFORMATION

Tamper resistant for your protection. Use only if saftey seal is intact.

Contains no artificial flavors or colorants. No gluten added. Lactose-free.

Inactive ingredients

Inactive Ingredients: Magnesium stearate, Maltodextrin, Sucrose.

KEEP OUT OF REACH OF CHILDREN

Keep this and all medication out of reach of children.

PREGNANCY OR BREAST FEEDING

If pregnant or breastfeeding, ask a health professional before use.

PURPOSE

Supports a positive outlook*

*Claims based on traditional homeopathic practice, not accepted medical evidence. Not FDA evaluated.